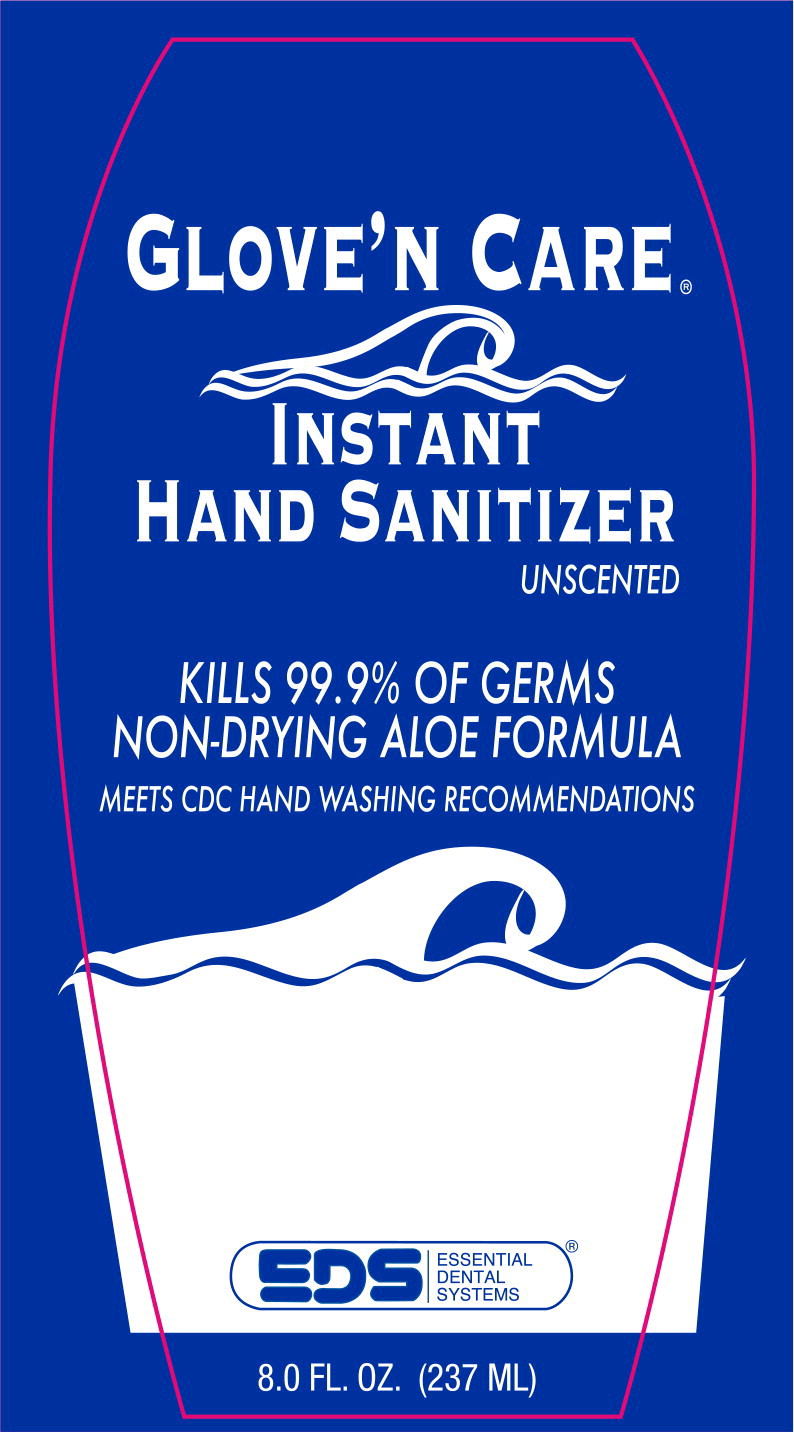 DRUG LABEL: Instant Hand Sanitizer
NDC: 73375-7800 | Form: GEL
Manufacturer: Essential Dental Systems Inc.
Category: otc | Type: HUMAN OTC DRUG LABEL
Date: 20230113

ACTIVE INGREDIENTS: alcohol 665 mL/1 L
INACTIVE INGREDIENTS: aloe vera leaf; CARBOMER HOMOPOLYMER TYPE C (ALLYL PENTAERYTHRITOL CROSSLINKED); water; trolamine

Drug Facts

Active ingredient

Ethyl Alcohol 66.5%

Purpose

Antiseptic

Uses

- for handwashing to decrease bacteria on skin
- recommended for repeated use

Warnings

For external use only

Flammable, keep away from fire or flame

Do not use In the eyes. If this happens, rinse thoroughly with water

Stop use and ask a doctor if irritation and redness develop and persists for more than 72 hours

Keep out of reach of children

If ingested get medical help or contact a Poison Control Center right away

Directions

- wet hands thoroughly with product
- allow to dry without wiping
- children under 6 should be supervised while using this product

Inactive ingredients

aloe vera, carbomer, purified water, triethanolamine

Principal Display Panel - 0.237 L Bottle Label

GLOVE'N CARE®

INSTANT
HAND SANITIZER

UNSCENTED

KILLS 99.9% OF GERMS

NON-DRYING ALOE FORMULA

MEETS CDC HAND WASHING RECOMMENDATIONS

EDS

ESSENTIAL
DENTAL
SYSTEMS

®

8.0 FL. OZ. (237 ML)